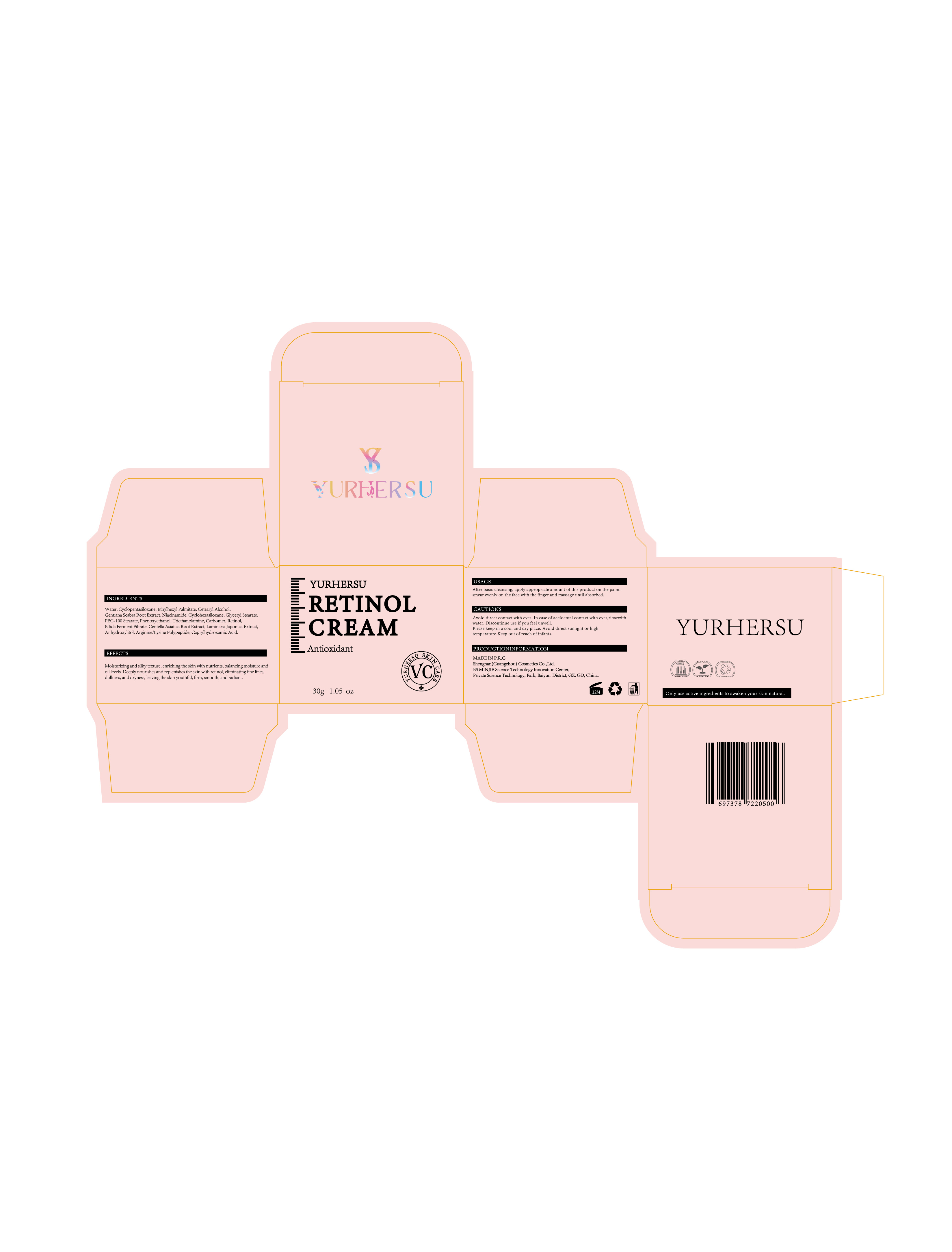 DRUG LABEL: RerinolCream
NDC: 84019-011 | Form: CREAM
Manufacturer: Shengnan (Guangzhou) Cosmetics Co., Ltd
Category: otc | Type: HUMAN OTC DRUG LABEL
Date: 20241123

ACTIVE INGREDIENTS: RETINOL 100 mg/1 g
INACTIVE INGREDIENTS: WATER; CYCLOPENTASILOXANE

RerinolCream

WARNINGS

Avoid direct contact with eyes. If accidentally in contact with eyes, rinse with water.

PURPOSE

Eliminate fine lines, dullness, and dryness, leaving the skin youthful, firm, smooth, and radiant.

Stop use and ask doctor if rash occurs,

ACTIVE INGREDIENT

Retinol

WHEN USING

Do not apply to wounds or damaged skin

INACTIVE INGREDIENT

Water,Cyclopentasiloxane,Ethylhexyl Palmitate,Cetearyl Alcohol,Gentiana Scabra Root Extract,Niacinamide,Cyclohexasiloxane,Glyceryl Stearate,PEG-100 Stearate,Phenoxyethanol,Triethanolamine,Carbomer,Bifida Ferment Filtrate,Centella Asiatica Root Extract,Laminaria Japonica Extract,Anhydroxylitol,Arginine/Lysine Polypeptide,Caprylhydroxamic Acid

DOSAGE AND ADMINISTRATION

Apply 1-2 times a day

INDICATIONS AND USAGE

After basic cleansing, apply appropriate amount of this product on the palm.
smear evenly on the face with the finger and massage until absorbed.